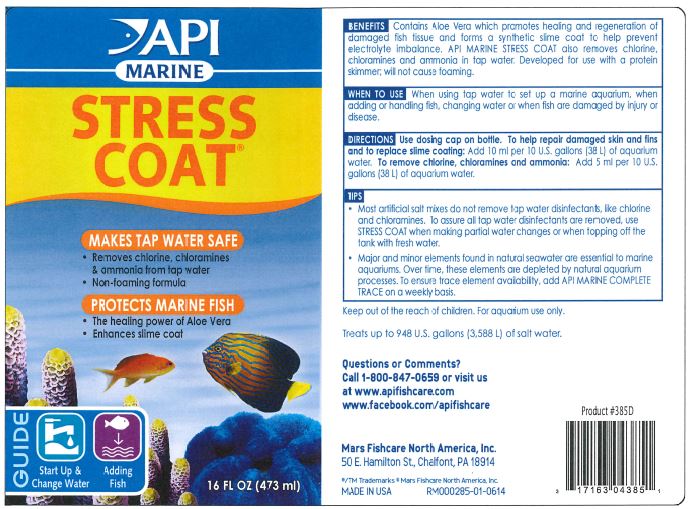 DRUG LABEL: API MARINE STRESS COAT
NDC: 17163-385 | Form: LIQUID
Manufacturer: MARS FISHCARE NORTH AMERICA, INC
Category: animal | Type: OTC ANIMAL DRUG LABEL
Date: 20191219

ACTIVE INGREDIENTS: ALOE VERA LEAF 0.05 g/100 mL

Drug Facts

DESCRIPTION

BENEFITS

Contains Aloe Vera which promotes healing and regeneration of damaged fish tissue and forms a synthetic slime coat to help prevent electrolyte imbalance.

API MARINE STRESS COAT also removes chlorine, chloramines and ammonia in tap water.

Developed for use with a protein skimmer; will not cause foaming.

INDICATIONS AND USAGE

WHEN TO USE

When using tap water to set up a marine aquarium, when adding or handling fish, changing water or when fish are damaged by injury or disease.

DIRECTIONS

Use dosing cap on bottle.

To help repair damaged skin and fins and to replace slime coating: Add 10 ml per 10 u.s. (38 L) of aquarium water.

To remove chlorine, chloramines and ammonia: Add 5 ml per 10 U.S. gallons (38 L) of aquarium water.

WHEN USING

TIPS

Most artificial salt mixes do not remove tap water disinfectants, like chlorine and chloramines. To assure all tap water disinfectants are removed, use STRESS COAT when making partial water changes or when topping off the tank with fresh water.

Major and minor elements found in natural seawater are essential to marine aquariums. Over time, these elements are depleted by natural aquarium processes. To ensure trace element availability, add API MARINE COMPLETE TRACE on a weekly basis.

WARNINGS AND PRECAUTIONS

Keep out of the reach of children.

For aquarium use only.

INFORMATION FOR OWNERS/CAREGIVERS

Treats up to 948 U.S. gallons (3,588 L) of salt water.

Questions or Comments?

Call 1-800-847-0659 or visit us

at www.apifishcare.com

www.facebook.com/apifishcare

PACKAGE LABEL

API

MARINE

STRESS

COAT

MAKES TAP WATER SAFE

Removes chlorine, chloramines

and ammonia from tap water

Non-foaming formula

PROTECTS MARINE FISH

The healing power of Aloe Vera

Enhances slime coat

Guide

Start Up and Change Water

Adding Fish

16 FL OZ (473 ml)